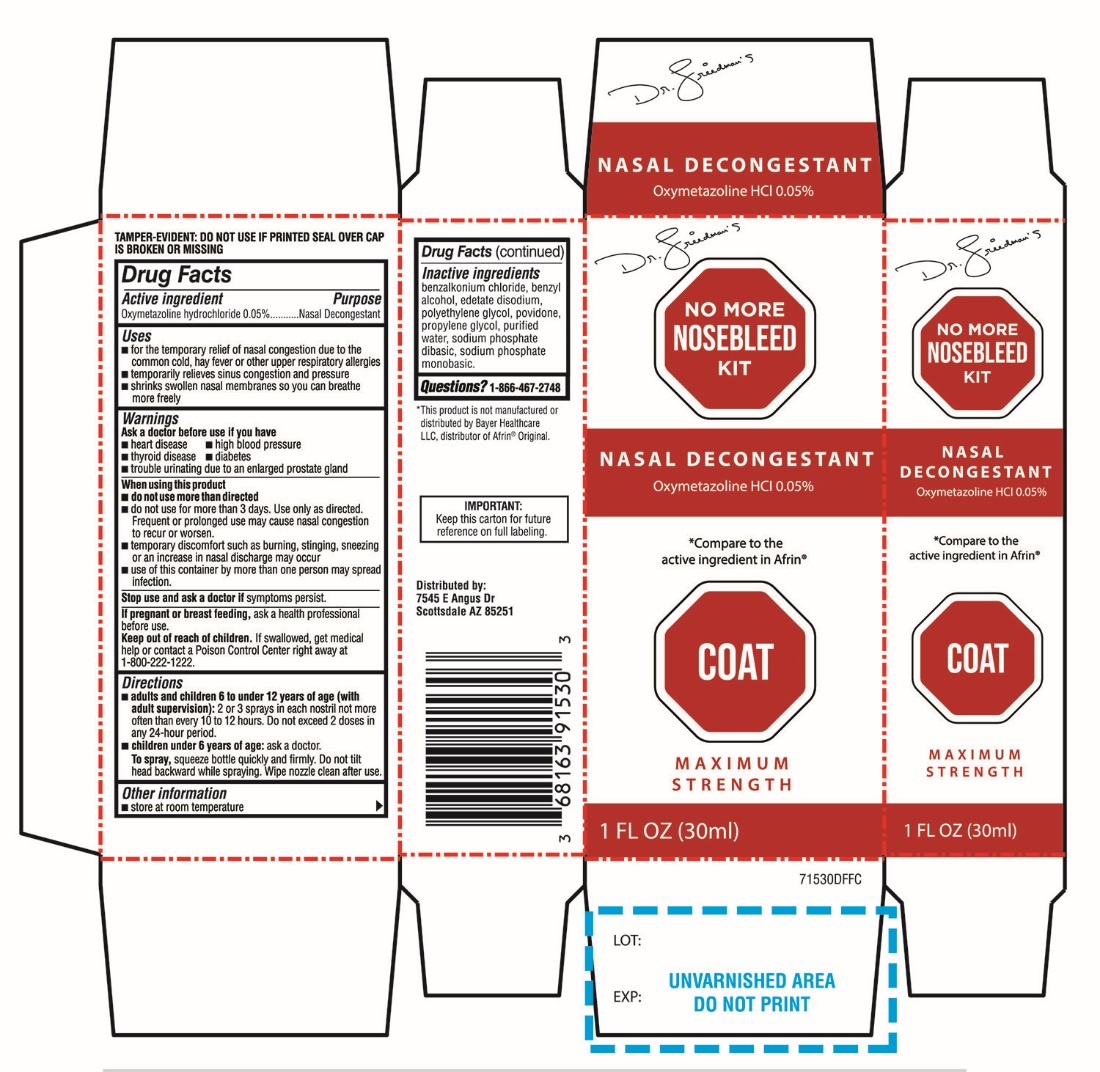 DRUG LABEL: NO MORE NOSEBLEED
NDC: 73169-001 | Form: LIQUID
Manufacturer: DR. FRIEDMAN'S NO MORE NOSEBLEED KIT INC.
Category: otc | Type: HUMAN OTC DRUG LABEL
Date: 20250911

ACTIVE INGREDIENTS: OXYMETAZOLINE HYDROCHLORIDE 0.05 g/100 mL
INACTIVE INGREDIENTS: BENZALKONIUM CHLORIDE; BENZYL ALCOHOL; EDETATE DISODIUM; POLYETHYLENE GLYCOL, UNSPECIFIED; POVIDONE, UNSPECIFIED; PROPYLENE GLYCOL; WATER; SODIUM PHOSPHATE, DIBASIC, ANHYDROUS; SODIUM PHOSPHATE, MONOBASIC, ANHYDROUS

NO MORE NOSEBLEED KIT NASAL DECONGESTANT

Active ingredient

Oxymetazoline hydrochloride 0.05%

Purpose

Nasal Decongestant

Uses

- for the temporary relief of nasal congestion due to the common cold, hay fever or other upper respiratory allergies.
- temporary relieves sinus congestion and pressure
- shrinks swollen nasal membranes so you can breathe more freely

Warnings

Ask a doctor before use if you have

- heart disease
- high blood pressure
- thyroid disease
- diabetes
- trouble urinating due to enlarged prostate gland

When using this product

- do not use more than directed
- do not use for more than 3 days. Use only as directed. Frequent or prolonged use may cause nasal congestion to recur or worsen
- temporary discomfort such as burning, stinging, sneezing or an increase in nasal discharge may occur
- use of this container by more than one person may spread infection.
- Stop use and ask a doctor ifsymptoms persist.
- If pregnant or breast feeding,ask a health professional before use.

Keep Out of Reach of Children

If swallowed, get medical help or contact a Poison Control Centre right away at 1-800-222-1222.

Directions

- adults and children 6 to under 12 years of age (with adult supervision):2 or 3 sprays in each nostril not more often than every 10 to 12 hours. Do not exceed 2 doses in any 24-hour period.
- Children under 6 years of age: ask a doctor.
- To spray, squeeze bottle quickly and firmly. Do not tilt head backward while spraying. Wipe nozzle clean after use.

Other information

- store at room temperature.

Inactive ingredients

benzalkonium Chloride, benzyl Alcohol, edetate disodium, polyethylene glycol, Povidone, propylene glycol, Purified water, Sodium Phosphate dibasic, Sodium Phosphate monobasic.